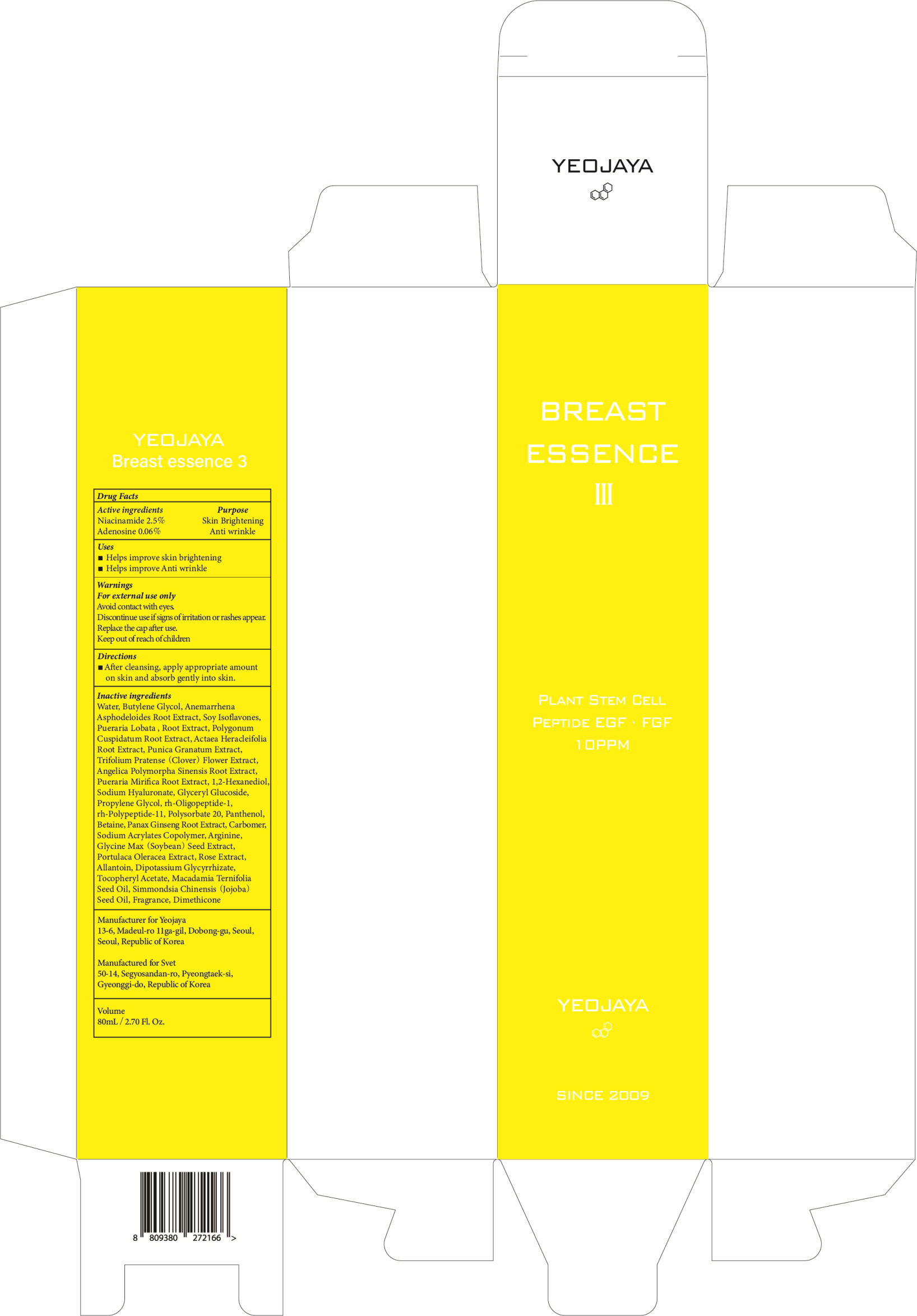 DRUG LABEL: Breast Essence III
NDC: 69142-010 | Form: CREAM
Manufacturer: yeojaya
Category: otc | Type: HUMAN OTC DRUG LABEL
Date: 20180917

ACTIVE INGREDIENTS: Niacinamide 2.0 g/80 mL; Adenosine 0.04 g/80 mL
INACTIVE INGREDIENTS: WATER; BUTYLENE GLYCOL

ACTIVE INGREDIENT

Active ingredients: Niacinamide 2.5%, Adenosine 0.06%

INACTIVE INGREDIENT

Inactive ingredients:

Water, Butylene Glycol, Anemarrhena Asphodeloides Root Extract, Soy Isoflavones, Pueraria Lobata , Root Extract, Polygonum Cuspidatum Root Extract, Actaea Heracleifolia Root Extract, Punica Granatum Extract, Trifolium Pratense (Clover) Flower Extract, Angelica Polymorpha Sinensis Root Extract, Pueraria Mirifica Root Extract, 1,2-Hexanediol, Sodium Hyaluronate, Glyceryl Glucoside, Propylene Glycol, rh-Oligopeptide-1, rh-Polypeptide-11, Polysorbate 20, Panthenol, Betaine, Panax Ginseng Root Extract, Carbomer, Sodium Acrylates Copolymer, Arginine, Glycine Max (Soybean) Seed Extract, Portulaca Oleracea Extract, Rose Extract, Allantoin, Dipotassium Glycyrrhizate, Tocopheryl Acetate, Macadamia Ternifolia Seed Oil, Simmondsia Chinensis (Jojoba) Seed Oil, Fragrance, Dimethicone

PURPOSE

Purpose: Skin Brightening, Anti wrinkle

WARNINGS

- For external use only

- Avoid contact with eyes.

- Discontinue use if signs of irritation or rashes appear.

- Replace the cap after use.

- Keep out of reach of children

KEEP OUT OF REACH OF CHILDREN

Uses

- Helps improve skin brightening

- Helps improve Anti wrinkle

Directions

- After cleansing, apply appropriate amount on skin and absorb gently into skin.